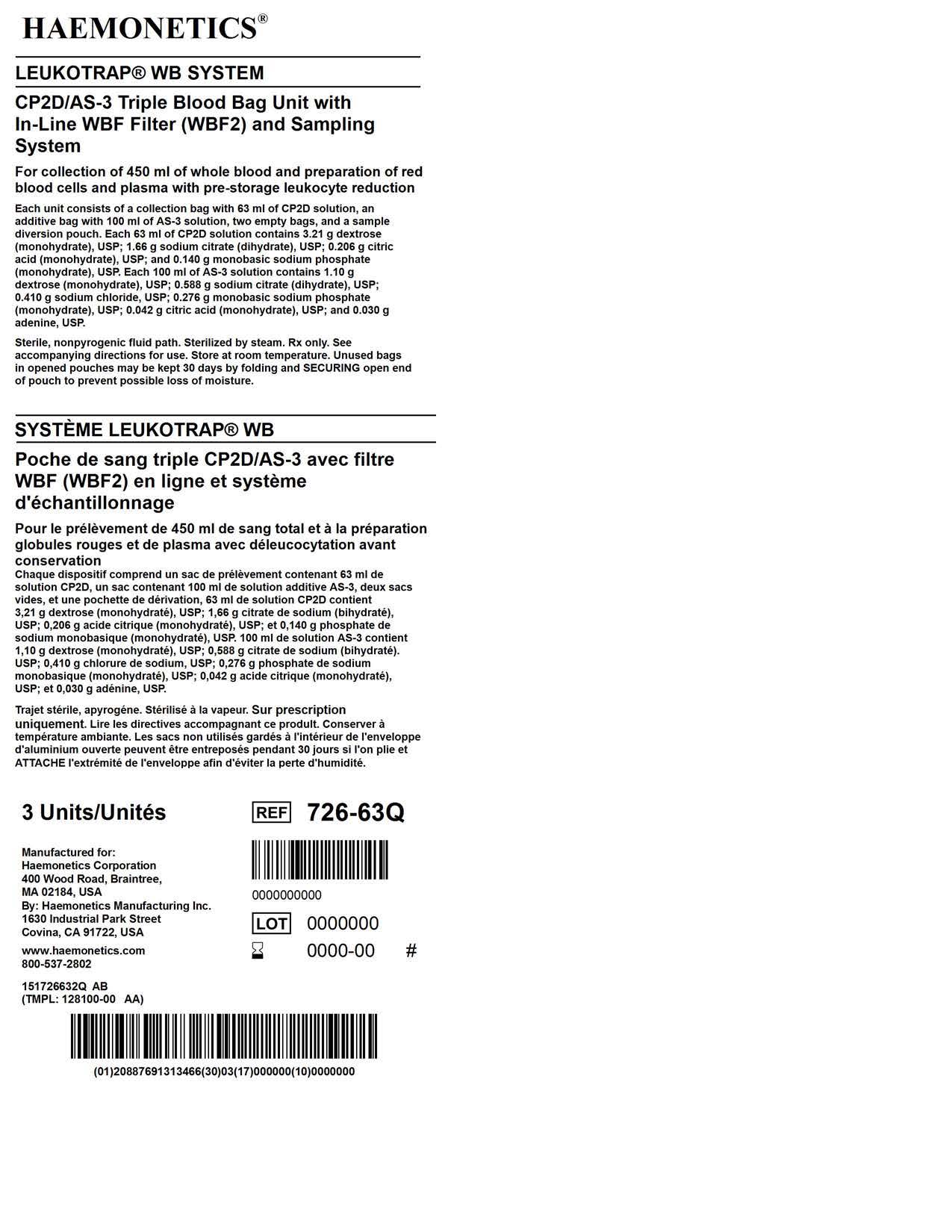 DRUG LABEL: Leukotrap WB System
NDC: 53157-262 | Form: KIT | Route: INTRAVENOUS
Manufacturer: Haemonetics Corporation
Category: prescription | Type: HUMAN PRESCRIPTION DRUG LABEL
Date: 20220126

ACTIVE INGREDIENTS: DEXTROSE 3.21 g/63 mL; ADENINE 0.03 g/100 mL; DEXTROSE 1.1 g/100 mL
INACTIVE INGREDIENTS: CITRIC ACID MONOHYDRATE 0.206 g/63 mL; SODIUM CITRATE 1.66 g/63 mL; SODIUM PHOSPHATE, MONOBASIC, MONOHYDRATE 0.14 g/63 mL; SODIUM PHOSPHATE, MONOBASIC, MONOHYDRATE 0.276 g/100 mL; SODIUM CITRATE 0.588 g/100 mL; SODIUM CHLORIDE 0.41 g/100 mL; CITRIC ACID MONOHYDRATE 0.042 g/100 mL

Leukotrap WB Sytem

DOSAGE AND ADMINISTRATION

CP2D Anticoagulant Solution and AS-3 Solution may be used with Haemonetics
apheresis devices. See the Haemonetics Operation Manual for full operating
instructions.

Prior to use of the solutions, check the solutions for leaks by squeezing each of the
bags firmly. If leaks are found, discard the solution.